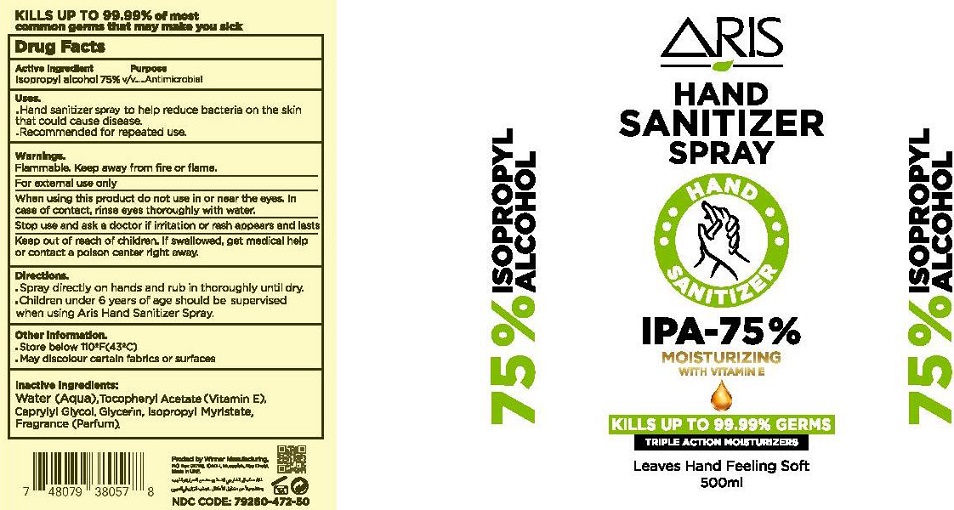 DRUG LABEL: Aris Hand Sanitizer
NDC: 79260-472 | Form: SPRAY
Manufacturer: WINNER MANUFACTURING
Category: otc | Type: HUMAN OTC DRUG LABEL
Date: 20200709

ACTIVE INGREDIENTS: ISOPROPYL ALCOHOL 75 mL/100 mL
INACTIVE INGREDIENTS: WATER; .ALPHA.-TOCOPHEROL ACETATE; CAPRYLYL GLYCOL; GLYCERIN; ISOPROPYL MYRISTATE

ARIS HAND SANITIZER SPRAY

Active Ingredient

Isopropyl alcohol 75% v/v

Purpose

Antimicrobial

Uses.

▪ Hand sanitizer spray to help reduce bacteria on the skin that could cause disease.

▪ Recommended for repeated use.

Warnings.

Flammable. Keep away from fire or flame

For external use only

When using this product do not use in or near the eyes. In case of contact, rinse eyes thoroughly with water.

Stop use and ask a doctor if irritation or rash appears and lasts

Keep out of reach of children. If swallowed, get medical help or contact a poison center right away.

Directions.

▪ Spray directly on hands and rub in thoroughly until dry.

▪ Children under 6 years of age should be supervised when using Aris Hand Sanitizer Spray.

Other Information.

▪ Store below 110°F(43°C)

▪ May discolour certain fabrics or surfaces

Inactive Ingredients

Water (Aqua), Tocopheryl Acetate (Vitamin E), Caprylyl Glycol, Glycerin, Isopropyl Myristate, Fragrance (Parfum).

MOISTURIZING WITH VITAMIN E

KILLS UP TO 99.99% GERMS

TRIPLE ACTION MOISTURIZERS

Leaves Hand Feeling Soft

KILLS UP TO 99.99% of most common germs that may make you sick

Produced by Winner Manufacturing

Made in UAE